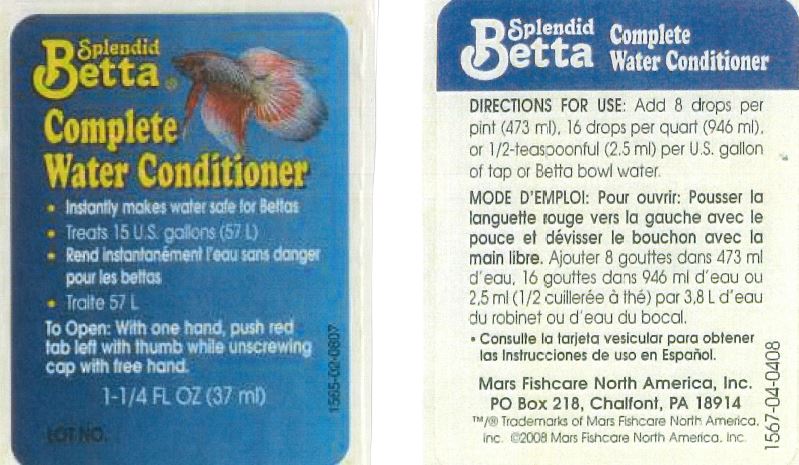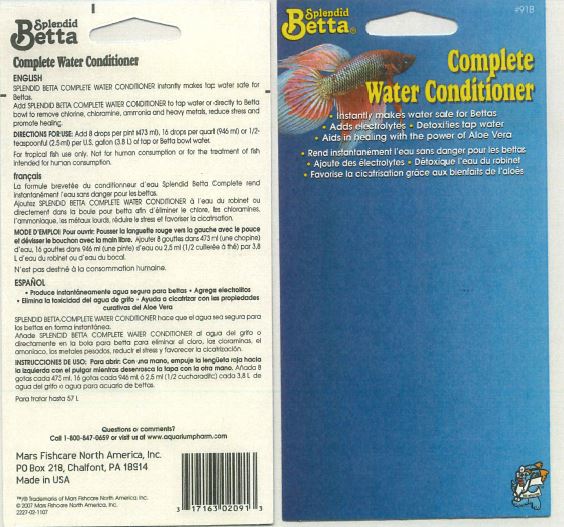 DRUG LABEL: Splendid Betta Complete Water Conditioner
NDC: 17163-091 | Form: LIQUID
Manufacturer: MARS FISHCARE NORTH AMERICA, INC
Category: animal | Type: OTC ANIMAL DRUG LABEL
Date: 20191219

ACTIVE INGREDIENTS: ALOE VERA LEAF 0.01 g/100 mL

Drug Facts

DESCRIPTION

SPLENDID BETTA COMPLETE WATER CONDITIONER Instantly makes tap water safe for Bettas.

INDICATIONS AND USAGE

Add SPLENDID BETTA COMPLETE WATER CONDITIONER to tap water or directly to Betta bowl to remove chlorine, chloramine, ammonia and heavy metals, reduce stress and promote healing.

DOSAGE AND ADMINISTRATION

DIRECTIONS FOR USE:

Add 8 drops per pint (473 ml), 16 drops per quart (946 ml), or 1/2-teaspoon (2.5 ml) per U.S. gallon of tap or Betta bowl water.

WARNINGS AND PRECAUTIONS

For tropical fish use only.

Not for human consumption or for the treatment of fish intended for human consumption.

Questions or comments?

Call 1-800-847-0659 or visit us at www.aquariumpharm.com

PACKAGE LABEL

Splendid

Betta

Complete

Water Conditioner

Instantly makes water safe for Bettas

Adds electrolytes

Detoxifies tap water

Aids in healing with the power of Aloe Vera

Treats 15 U.S. gallons (57 L)

To Open: With one hand, push red

tab left with thumb while unscrewing cap with free hand.

1-1/4 FL OZ (37 ml)

Lot No.